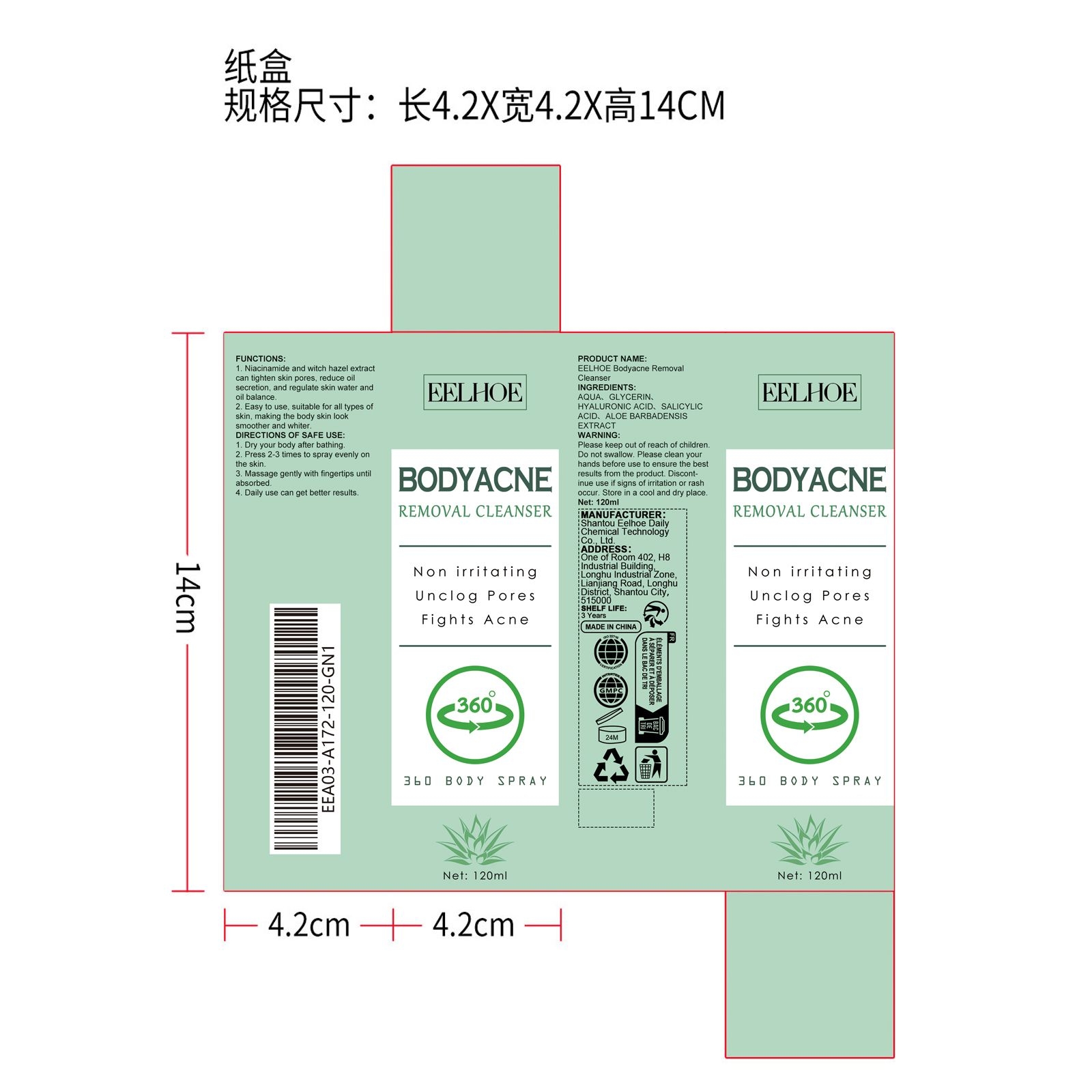 DRUG LABEL: EELHOE Bodyacne Removal Cleanser
NDC: 85064-010 | Form: LIQUID
Manufacturer: Shantou Eelhoe Daily Chemical Technology Co., Ltd.
Category: otc | Type: HUMAN OTC DRUG LABEL
Date: 20251127

ACTIVE INGREDIENTS: ALOE BARBADENSIS LEAF 0.024 mg/120 mg
INACTIVE INGREDIENTS: HYALURONIC ACID 0.024 mg/120 mg; AQUA 115.128 mg/120 mg; GLYCERIN 4.8 mg/120 mg; SALICYLIC ACID 0.024 mg/120 mg

ACTIVE INGREDIENT

ALOE BARBADENSIS EXTRACT

WHEN USING

1. Dry your body after bathing

2. Press 2-3 times to spray evenly on the skin

3. Massage gently with fingertips until absorbed

4. Daily use can get better results

PURPOSE

1. Niacinamide and witch hazel extract can tighten skin pores, reduce oil secretion, and regulate skin water and oil balance.

2. Easy to use, suitable for all types of skin, making the body skin look smoother and whiter.

WARNINGS

Please keep out of reach of children. Do not swallow. Please clean your hands before use to ensure the best results from the product. Discontinue use if signs of irritation or rash occur. Store in a cool and dry place.

DO NOT USE

Discontinue use if signs of irritation or rash occur.

STOP USE

Discontinue use if signs of irritation or rash occur.

KEEP OUT OF REACH OF CHILDREN

Please keep out of reach of children. Do not swallow.

STORAGE AND HANDLING

Store in a cool and dry place.

INACTIVE INGREDIENT

AQUA、GLYCERIN、HYALURONIC ACID、SALICYLIC ACID

DOSAGE AND ADMINISTRATION

Press 2-3 times to spray evenly on the skin

INDICATIONS AND USAGE

Massage gently with fingertips until absorbed